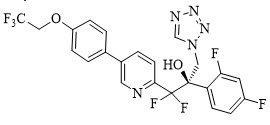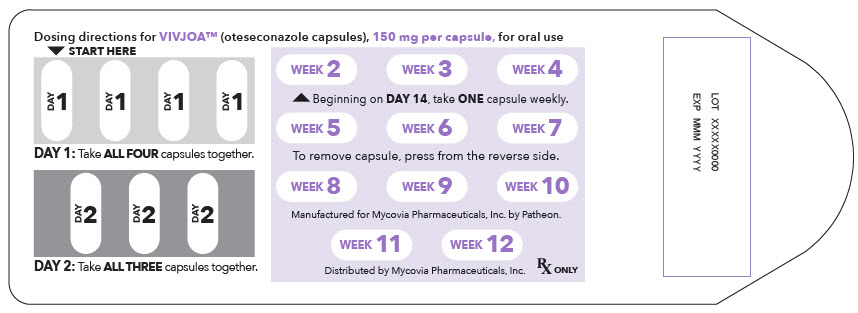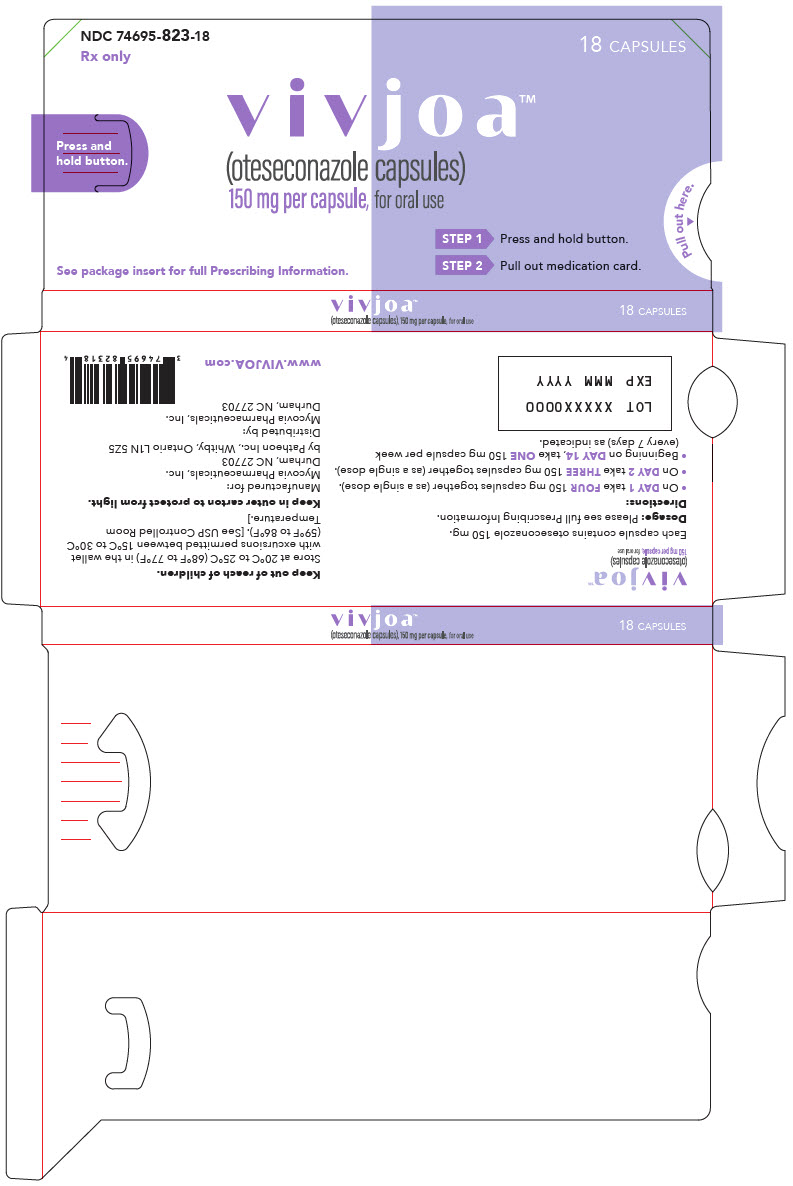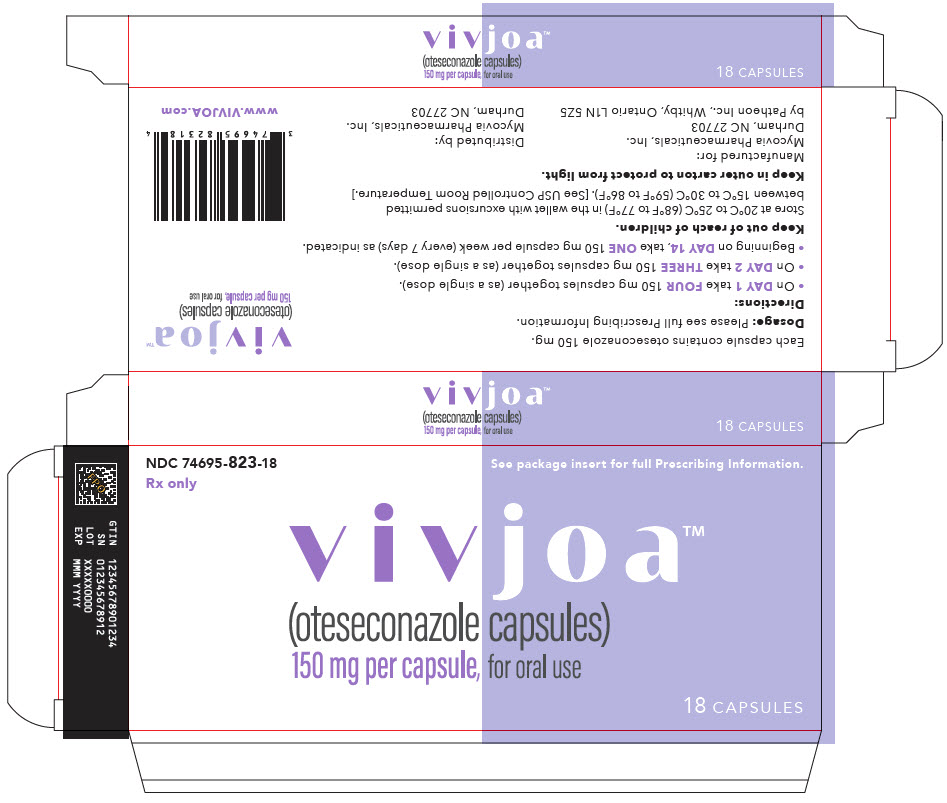 DRUG LABEL: VIVJOA
NDC: 74695-823 | Form: CAPSULE
Manufacturer: Mycovia Pharmaceuticals, Inc.
Category: prescription | Type: HUMAN PRESCRIPTION DRUG LABEL
Date: 20260108

ACTIVE INGREDIENTS: OTESECONAZOLE 150 mg/1 1
INACTIVE INGREDIENTS: MICROCRYSTALLINE CELLULOSE 20 mg/1 1; SILICON DIOXIDE; LACTOSE MONOHYDRATE; CROSCARMELLOSE SODIUM; HYDROXYPROPYL CELLULOSE (90000 WAMW); SODIUM LAURYL SULFATE; MAGNESIUM STEARATE

HIGHLIGHTS OF PRESCRIBING INFORMATION

These highlights do not include all the information needed to use VIVJOA™ safely and effectively. See full prescribing information for VIVJOA™.
VIVJOA™ (oteseconazole) capsules, for oral use
Initial U.S. Approval: 2022

1 INDICATIONS AND USAGE

VIVJOA™ is an azole antifungal indicated to reduce the incidence of recurrent vulvovaginal candidiasis (RVVC) in females with a history of RVVC who are NOT of reproductive potential. (1)

2 DOSAGE AND ADMINISTRATION

- There are two recommended VIVJOA dosage regimens: a VIVJOA-only regimen and a Fluconazole/VIVJOA regimen. Use one of these two dosage regimens. (2.1)
  - Administer VIVJOA orally with food. (2.1)
- For the VIVJOA-only Dosage Regimen: (2.2)
  - On Day 1:Administer VIVJOA 600 mg (as a single dose), then
  - On Day 2:Administer VIVJOA 450 mg (as a single dose), then
  - Beginning on Day 14: Administer VIVJOA 150 mg once a week (every 7 days) for 11 weeks (Weeks 2 through 12).
- For the Fluconazole/VIVJOA Dosage Regimen, prescribe fluconazole and: (2.3)
  - On Day 1, Day 4, and Day 7: Administer fluconazole 150 mg orally,then
  - On Days 14 through 20: Administer VIVJOA 150 mg once daily for 7 days, then
  - Beginning on Day 28: Administer VIVJOA 150 mg once a week (every 7 days) for 11 weeks (Weeks 4 through 14).

3 DOSAGE FORMS AND STRENGTHS

Capsules:150 mg of oteseconazole (fluconazole is not supplied in the carton). (3)

4 CONTRAINDICATIONS

- Females of Reproductive Potential (4), (5.1), (8.3)
- Pregnant and Lactating women (4), (8.1), (8.2)
- Hypersensitivity to oteseconazole (4)

5 WARNINGS AND PRECAUTIONS

Embryo-Fetal Toxicity:Based on animal studies, VIVJOA may cause fetal harm. The drug exposure window of approximately 690 days (based on 5 times the half-life of oteseconazole) precludes adequate mitigation of the embryo-fetal toxicity risks. Advise patients that VIVJOA is contraindicated in females of reproductive potential, and in pregnant and lactating women because of potential risks to a fetus or breastfed infant. (5.1, 8.1, 8.2, 8.3)

6 ADVERSE REACTIONS

The most frequently reported adverse reactions (incidence > 2%) were headache and nausea. (6.1)

To report SUSPECTED ADVERSE REACTIONS, contact Mycovia Pharmaceuticals, Inc. at 1-855-299-0637 or FDA at 1-800-FDA-1088 or www.fda.gov/medwatch.

7 DRUG INTERACTIONS

BCRP (Breast Cancer Resistance Protein) Substrates:Concomitant use of VIVJOA with BCRP substrates may increase the exposure of drugs that are BCRP substrates, which may increase the risk of adverse reactions associated with these drugs. Use the lowest possible starting dose of the BCRP substrate or consider reducing the dose of the substrate drugs and monitor for adverse reactions. (7.1)

8 USE IN SPECIFIC POPULATIONS

- Renal Impairment:Not recommended in severe renal impairment or ESRD (with or without dialysis). (8.6)
- Hepatic Impairment:Not recommended in moderate or severe hepatic impairment. (8.7)

FULL PRESCRIBING INFORMATION

1 INDICATIONS AND USAGE

1.1 Vulvovaginal Candidiasis

VIVJOA is indicated to reduce the incidence of recurrent vulvovaginal candidiasis (RVVC) in females with a history of RVVC who are NOT of reproductive potential [see Warnings and Precautions (5.1), Use in Specific Populations (8.3), and Clinical Studies (14)] .

1.2 Usage

If specimens for fungal culture are obtained prior to therapy, antifungal therapy may be instituted before the results of the cultures are known. However, once these results become available, antifungal therapy should be adjusted accordingly.

2 DOSAGE AND ADMINISTRATION

2.1 Dosage Overview and Important Administration Instructions

There are two recommended VIVJOA dosage regimens: a VIVJOA-only regimen and a Fluconazole/ VIVJOA regimen. Use one of the following two dosage regimens:

- VIVJOA-only dosage regimen [see Dosage and Administration (2.2)]
- Fluconazole/VIVJOA dosage regimen [see Dosage and Administration (2.3)] .

Administer VIVJOA orally with food [see Clinical Pharmacology (12.3)]. Swallow the capsules whole. Do not chew, crush, dissolve, or open the capsules.

2.2 VIVJOA-only Dosage Regimen

For the VIVJOA-only dosage regimen:

- On Day 1:Administer VIVJOA 600 mg (as a single dose), then
- On Day 2:Administer VIVJOA 450 mg (as a single dose), then
- Beginning on Day 14:Administer VIVJOA 150 mg once a week (every 7 days) for 11 weeks (Weeks 2 through 12).

2.3 Fluconazole/VIVJOA Dosage Regimen

For the Fluconazole/VIVJOA dosage regimen, prescribe fluconazole and:

- On Day 1, Day 4, and Day 7:Administer fluconazole 150 mg orally, then
- On Days 14 through 20:Administer VIVJOA 150 mg once daily for 7 days, then
- Beginning on Day 28:Administer VIVJOA 150 mg once a week (every 7 days) for 11 weeks (Weeks 4 through 14).

3 DOSAGE FORMS AND STRENGTHS

VIVJOA Capsules: 150 mg of oteseconazole in lavender hard gelatin capsules imprinted with OTE 150 in black ink.

Fluconazole is not supplied in the carton.

4 CONTRAINDICATIONS

VIVJOA is contraindicated in:

- Females of reproductive potential [see Warnings and Precautions (5.1)and Use in Specific Populations (8.3)]
- Pregnant and lactating women [see Warnings and Precautions (5.1), and Use in Specific Populations (8.1, 8.2)]
- Patients with known hypersensitivity to oteseconazole.

5 WARNINGS AND PRECAUTIONS

5.1 Embryo-Fetal Toxicity

VIVJOA is contraindicated in females of reproductive potential, and in pregnant and lactating women. Based on animal studies, VIVJOA may cause fetal harm. The drug exposure window of approximately 690 days (based on 5 times the half-life of oteseconazole) precludes adequate mitigation of the embryo-fetal toxicity risks. Ocular abnormalities were observed in the offspring of pregnant rats dosed at 7.5-mg/kg/day during organogenesis through lactation in pre and postnatal developmental studies. The observed ocular abnormalities included cataracts, opacities, exophthalmos/buphthalmos, optic nerve/retinal atrophy, lens degeneration and hemorrhage. Ocular abnormalities occurred at doses about 3.5 times the steady state clinical exposure seen with patients being treated for RVVC. Advise patients that VIVJOA is contraindicated in females of reproductive potential, and in pregnant and lactating women because of potential risks to a fetus or breastfed infant [see Use in Specific Populations (8.1, 8.2, 8.3)].

6 ADVERSE REACTIONS

6.1 Clinical Trials Experience

Because clinical trials are conducted under widely varying conditions, adverse reaction rates observed in the clinical trials of one drug cannot be directly compared to rates in the clinical trials of another drug and may not reflect the rates observed in practice.

A total of 580 patients were treated with VIVJOA in three clinical trials (Trial 1, Trial 2, and Trial 3) [see Clinical Studies (14)] . Patients in the clinical trials were women with RVVC who received VIVJOA treatment for 12 weeks. The mean age of the patient population was 34 years (range:16-78 years), with 84% of patients aged 18-44 years and 16% of patients aged 45 years and older. Although females of reproductive potential were included in the clinical safety data, VIVJOA is contraindicated in females of reproductive potential due to the risk of embryo-fetal toxicity [see Contraindications (4), Warnings and Precautions (5.1), and Use in Specific Populations (8.1, 8.3, 8.4)] .

The clinical trials population was 75% (435/580) White, 17% (96/580) Black or African American, 6% (36/580) Asian, and 2% (13/580) Other women. Fifteen percent (86/580) of all women were Hispanic/Latino. Patients enrolled in the induction and maintenance phases of the clinical trials were treated with different VIVJOA dosage regimens versus comparators [see Clinical Studies (14)] .

The adverse reaction that led to discontinuation in 1 of 580 (0.2 %) VIVJOA-treated patients was allergic dermatitis. Overall, similar percentages of serious adverse reactions and adverse reactions leading to drug discontinuation were reported across the VIVJOA and comparator patient dosing groups.

The most frequently reported adverse reactions (incidence >2%) among VIVJOA-treated patients in Trial 1, Trial 2 and Trial 3 were headache (includes headache, migraines, sinus headaches) (7.4%) and nausea (3.6%).

Other Adverse Reactions

The following selected adverse reactions occurred in <2% of patients receiving VIVJOA in Trial 1, Trial 2 and Trial 3:

- Laboratory investigations:Increased blood creatine phosphokinase
- Gastrointestinal disorders:Dyspepsia
- Vascular disorders:Hot flush
- Renal and urinary disorders:Dysuria
- Reproductive system and breast disorders:Menorrhagia (includes genital hemorrhage, menorrhagia; menometrorrhagia; uterine hemorrhage, vaginal hemorrhage) metrorrhagia; vulvovaginal irritation (includes vulvovaginal burning sensation, vulvovaginal discomfort, and vulvovaginal pain)

Laboratory Findings

Elevations in Creatine Phosphokinase

Serum creatine phosphokinase (CPK) (an indirect marker of muscle injury/necrosis) elevations greater than or equal to 10 times the upper limit of normal were observed in 11 (1.9%) patients treated with VIVJOA versus 2 (0.7%) patients in the comparator groups during the VIVJOA clinical trials. The elevations were transient.

7 DRUG INTERACTIONS

7.1 Effect of VIVJOA on Other Drugs

BCRP (Breast Cancer Resistance Protein) Transporter Substrates

Oteseconazole is a BCRP inhibitor. Concomitant use of VIVJOA with BCRP substrates (e.g., rosuvastatin) may increase the exposure of BCRP substrates (e.g., rosuvastatin), which may increase the risk of adverse reactions associated with these drugs. Use the lowest possible starting dose of the BCRP substrate or consider reducing the dose of the substrate drug and monitor for adverse reactions [see Clinical Pharmacology (12.3)] .

8 USE IN SPECIFIC POPULATIONS

8.1 Pregnancy

Risk Summary

VIVJOA is contraindicated in females of reproductive potential and in pregnant women. Based on animal studies, VIVJOA may cause fetal harm when administered to pregnant women. In addition, the drug exposure window of approximately 690 days (based on 5 times the half-life of oteseconazole) precludes adequate mitigation of the embryo-fetal toxicity risks [see Warnings and Precautions (5.1)and Clinical Pharmacology (12.3)].

Ocular abnormalities were observed in a pre and postnatal animal study in the offspring of rats administered oteseconazole from Gestation Day 6 through Lactation Day 20 at doses about 3.5 times the recommended human dose based on AUC comparisons (see Data). The observed ocular abnormalities included cataracts, opacities, exophthalmos/buphthalmos, optic nerve/retinal atrophy, lens degeneration and hemorrhage.

There are limited human data in pregnant women who were exposed to VIVJOA during the clinical trials; these data are insufficient to exclude a potential risk of cataracts or other eye abnormalities in human infants.

Data

Animal Data

Rat and rabbit embryofetal development was assessed after oral administration of oteseconazole. There was no embryofetal toxicity or malformations at 40 mg/kg/day following administration of oteseconazole during organogenesis in pregnant rats at doses about 10 times the maximum human exposure for RVVC based on AUC comparisons. Abortions occurred in rabbits in the presence of maternal toxicity (reduced bodyweight gain with reduced food consumption) but there were no malformations at 15 mg/kg/day following administration of oteseconazole during organogenesis in pregnant rabbits about 6 times the maximum human exposure for RVVC based on AUC comparisons.

Ocular abnormalities including cataracts, opacities, exophthalmos/buphthalmos, optic nerve/retinal atrophy, lens degeneration and hemorrhage were observed in the offspring of rats administered oteseconazole from Gestation Day 6 through Lactation Day 20 at 7.5 mg/kg day (about 3.5 times the recommended human dose based on AUC comparisons). There were no effects on pregnancy or parturition in these pre and postnatal studies at any dose.

8.2 Lactation

Risk Summary

VIVJOA is contraindicated in lactating women and females of reproductive potential. There are no data on the presence of oteseconazole in human or animal milk or data on the effects of oteseconazole on milk production. There were no reported adverse effects in breastfed infants following maternal exposure to oteseconazole during lactation; however, given the limited duration of follow-up of the oteseconazole-exposed infants during the post-natal period, no conclusions can be drawn from these data [see Warnings and Precautions (5.1)] .

Ocular abnormalities were observed in a pre and postnatal study in the offspring of rats administered oteseconazole from Gestation Day 6 through Lactation Day 20 at doses approximately 3.5 times the recommended human dose based on AUC comparisons [see Use in Specific Populations (8.1)]. The relationship between the observed animal findings and breastfed infants is unknown.

8.3 Females of Reproductive Potential

VIVJOA is contraindicated in females of reproductive potential based on animal findings. The drug exposure window of approximately 690 days (based on 5 times the half-life of oteseconazole) precludes adequate mitigation of the embryo-fetal toxicity risks [see Warnings and Precautions (5.1), Use in Specific Populations (8.1)and Clinical Pharmacology (12.3)].

Females who are NOT of reproductive potential are defined as: persons who are biological females who are postmenopausal or have another reason for permanent infertility (e.g., tubal ligation, hysterectomy, salpingo-oophorectomy).

8.4 Pediatric Use

VIVJOA is contraindicated in females of reproductive potential. Based on animal studies, VIVJOA may cause fetal harm when administered to a pregnant woman or potential harm to the breastfed infant. The drug exposure window of approximately 690 days (based on 5 times the half-life of oteseconazole) precludes adequate mitigation of the embryo-fetal toxicity risks associated with VIVJOA use [see Contraindications (4), Warnings and Precautions (5.1)and Use in Specific Populations (8.1, 8.2, 8.3)and Clinical Pharmacology (12.3)] .

The safety and effectiveness of VIVJOA have not been established in pre-menarchal pediatric females.

8.5 Geriatric Use

Clinical studies of VIVJOA did not include sufficient numbers of patients 65 years of age and older to determine whether they respond differently from younger adult patients.

8.6 Renal Impairment

No dosage adjustment of VIVJOA is recommended in patients with mild to moderate renal impairment (i.e., estimated glomerular filtration rate (eGFR) by the modification of diet in renal disease (MDRD) equation 30-89 mL/min). Clinical studies of VIVJOA did not include sufficient numbers of patients with severe renal impairment (eGFR 15-29 mL/min) or end-stage renal disease (ESRD), defined as eGFR <15 mL/min, to determine the safety of VIVJOA in this population. Therefore, VIVJOA is not recommended for use in patients with severe renal impairment or ESRD (with or without dialysis) [see Clinical Pharmacology (12.3)].

8.7 Hepatic Impairment

No dosage adjustment of VIVJOA is recommended in patients with mild hepatic impairment (Child-Pugh A). There is insufficient information to determine the safety of VIVJOA in patients with moderate or severe hepatic impairment (Child-Pugh B-C). Therefore, VIVJOA is not recommended for use in patients with moderate or severe hepatic impairment [see Clinical Pharmacology (12.3)].

11 DESCRIPTION

VIVJOA (oteseconazole capsules) contains oteseconazole which is an oral azole antifungal agent.

The chemical name of oteseconazole is (R)-2-(2,4-difluorophenyl)-1,1-difluoro-3-(1 H-tetrazol-1-yl)-1-(5-(4-(2,2,2-trifluoroethoxy)phenyl)pyridin-2-yl)propan-2-ol or 2-Pyridineethanol, α-(2,4-difluorophenyl)-β β-difluoro- α-(1 H-tetrazol-1-ylmethyl)-5-(4-(2,2,2-trifluoroethoxy)phenyl)-,(α R)-. The empirical formula is C23H16F7N5O2. The molecular weight is 527.39 g/mol. The structural formula is

Oteseconazole is a white to off-white crystalline powder and is practically insoluble in water within a pH range of 1 to 9 but is soluble in a variety of organic solvents.

Each oteseconazole capsule, for oral use, contains 150 mg oteseconazole and the following inactive ingredients: croscarmellose sodium, hydroxypropyl cellulose, lactose, magnesium stearate, silicified microcrystalline cellulose, and sodium lauryl sulfate. Capsule shell and print constituents: FD&C Blue #1, FD&C Red #3, gelatin, Opacode SW-9008/SW-9009 and titanium dioxide. Contains no ingredient made from a gluten-containing grain (wheat, barley, or rye).

12 CLINICAL PHARMACOLOGY

12.1 Mechanism of Action

Oteseconazole is an antifungal drug [see Microbiology (12.4)] .

12.2 Pharmacodynamics

Oteseconazole exposure-response relationships and the time course of pharmacodynamic response are unknown.

Cardiac Electrophysiology

At 5 times the maximum exposures for the recommended dose, VIVJOA does not prolong the QT interval to any clinically relevant extent.

12.3 Pharmacokinetics

The AUC of oteseconazole increased approximately dose proportionally while the Cmaxincreased less than dose proportionally over a dose range of 20 mg (0.13 times the lowest recommended dose) to 320 mg (0.53 times the highest recommended dose). The pharmacokinetic parameters of oteseconazole associated with the administration of the recommended dosing regimen of VIVJOA are presented in Table 1.

Table 1: Pharmacokinetic (PK) Parameters of Oteseconazole
PK Parameter [Following repeat dose administration of VIVJOA at the approved recommended dosage for RVVC at the end of treatment.] | Mean (± SD)
Cmax(µg/mL) | 2.8 (1.25)
AUC24h(h∙µg/mL) | 64.2 (29.4)
Cmin(µg/mL) | 2.5 (1.19)

Absorption

The time to peak plasma concentrations of oteseconazole was approximately 5 to 10 hours.

Effect of Food

Administration of VIVJOA with a high-fat, high-calorie meal (800-1000 Calories; 50% fat) increased Cmaxand AUC0-72hby 45% and 36%, but no significant differences were observed with a low-fat, low-calorie meal.

Distribution

The central volume of distribution of oteseconazole is approximately 423 L. Oteseconazole is 99.5-99.7% bound to plasma proteins. Animal studies indicated that oteseconazole exposures in vaginal tissue are comparable to plasma exposures.

Elimination

The median terminal half-life of oteseconazole is approximately 138 days.

Metabolism

Oteseconazole does not undergo significant metabolism.

Excretion

Following oral administration of radiolabeled oteseconazole, approximately 56% of the radiolabeled dose was recovered in feces primarily through biliary excretion and 26% was recovered in urine.

Specific Populations

There were no clinically significant differences in the pharmacokinetics of oteseconazole based on sex, race/ethnicity or mild to moderate renal impairment.

Drug Interaction Studies

BCRP substrates:Oteseconazole increased the Cmaxand AUC0-24hof rosuvastatin, a BCRP substrate, by 118% and 114%, respectively .

Other Drugs:No clinically significant differences in the pharmacokinetics of the following drugs were observed when co-administered with oteseconazole: Midazolam (sensitive CYP3A4 substrate), ethinyl estradiol (CYP3A4 substrate), norethindrone (CYP3A4 substrate), or digoxin (P-gp substrate).

12.4 Microbiology

Mechanism of Action:

Oteseconazole is an azole metalloenzyme inhibitor targeting the fungal sterol, 14α demethylase (CYP51), an enzyme that catalyzes an early step in the biosynthetic pathway of ergosterol, a sterol required for fungal cell membrane formation and integrity. Inhibition of CYP51 results in the accumulation of 14-methylated sterols, some of which are toxic to fungi. Through the inclusion of a tetrazole metal-binding group, oteseconazole has a lower affinity for human CYP enzymes.

Resistance:

The potential for increases in minimum inhibitory concentrations (MIC) to oteseconazole has been evaluated in vitroincluding specific mechanisms of resistance .Increases in oteseconazole MIC were associated with upregulation of the efflux pumps CDR1, MDR1, and the azole target, lanosterol 14-alpha-demethylase (CYP51). Against certain Candidaspp. oteseconazole maintained meaningful in vitroactivity against clinical isolates that were resistant to fluconazole.

Antimicrobial Activity:

The following in vitrodata is available, but their clinical significance is unknown. Oteseconazole has been shown to be active against most isolates of the following microorganisms associated with RVVC [see Indications and Usage (1.1)] :

- Candida albicans
- Candida glabrata
- Candida krusei
- Candida parapsilosis
- Candida tropicalis
- Candida lusitaniae
- Candida dubliniensis

13 NONCLINICAL TOXICOLOGY

13.1 Carcinogenesis, Mutagenesis, Impairment of Fertility

Carcinogenesis

There was no increase in the incidence of tumors following daily oral administration of oteseconazole to Tg.rasH2 mice for 6 months at doses of 5 mg/kg/day (males) and 15 mg/kg/day (females), which are up to 3 and 10 times, respectively, the maximum human exposure for RVVC based on AUC comparisons.

In an oral carcinogenicity study, Sprague Dawley rats were administered doses of 0.5, 1.5, or 5 mg/kg/day oteseconazole once daily for up to 90 weeks. The high dose was initially reduced from 5 to 3 mg/kg/day due to excess mortality in males and reduced body weight in females. In males, an increase in the incidence in Leydig cell adenomas of the testes and thyroid follicular cell adenomas/carcinomas (combined) were increased at ≥1.5 mg/kg/day (similar to the maximum human exposure for RVVC based on AUC comparisons). In females, thyroid follicular cell adenomas and carcinomas (combined) were increased at ≥1.5 mg/kg/day (similar to the maximum human exposure for RVVC based on AUC comparisons) and thyroid carcinomas were increased at 5 to 3 mg/kg/day (5 times the maximum human exposure for RVVC based on AUC comparisons). The Leydig and thyroid findings are of uncertain relevance to humans.

Mutagenesis

Oteseconazole was negative in the bacterial reverse mutation assay, in vitrochromosomal aberration assay and micronucleus assay in rats.

Impairment of Fertility

Male rats were administered daily oral doses of 0, 0.5, 3, or 10 mg/kg/day oteseconazole beginning 42 days prior to pairing with untreated females, through the mating and post-mating period until euthanasia on Day 76 of treatment followed by a 12-week recovery period. There were no effects on reproductive and/or fertility parameters at the time of mating at 10 mg/kg/day (7 times the maximum human exposure for RVVC based on AUC comparisons). Increased incidences of abnormal sperm were observed at 3 mg/kg/day and sperm counts were reduced at 10 mg/kg/day. Although fertility was unaffected, sperm concentration remained reduced at the end of the recovery period.

Female rats were administered daily oral doses of 0, 1.5, 5, or 25 mg/kg/day oteseconazole beginning 28 days prior to cohabitation with untreated males, continuing throughout mating and through gestational day 7. Although there were no effects on estrous cyclicity, effects on reproductive and fertility parameters were observed at 25 mg/kg/day in the presence of maternal toxicity (11 times the maximum human exposure for RVVC based on AUC comparisons).

13.2 Animal Toxicology and/or Pharmacology

In an oral carcinogenicity study, Sprague Dawley rats were administered doses of 0.5, 1.5, or 5 mg/kg/day oteseconazole once daily for up to 90 weeks. The high dose was initially reduced from 5 to 3 mg/kg/day in males due to excess mortality. Incidences of hemorrhage were increased in the adrenals, brain, coagulating gland, ears, epididymides, head, heart, lung, nose, pancreas, pharynx, prostate, seminal vesicles, spinal cord, testes, thymus, and bladder of male Crl:CD®(SD) rats (after 77 weeks of dosing at about 5 times the MRHD based on AUC comparisons). There were no increases in the incidence of hemorrhage in rats after 26 weeks at 5 mg/kg. The clinical relevance of these findings after very high doses (5 to 7 times the MRHD) for the lifetime of the rat remains unclear.

14 CLINICAL STUDIES

Overview of the Clinical Studies

A total of 656 adults and post-menarchal pediatric females with RVVC (defined as ≥3 episodes of vulvovaginal candidiasis (VVC) in a 12-month period) were randomized in two multicenter, multinational, double-blind, placebo-controlled trials: Trial 1 (NCT#03562156) and Trial 2 (NCT#03561701). A total of 219 adults and post-menarchal pediatric females with RVVC were randomized in a multicenter, double-blind trial [Trial 3 (NCT#03840616)]. Although females of reproductive potential were included in the clinical efficacy data, VIVJOA is contraindicated in females of reproductive potential due to the risk of embryo-fetal toxicity [see Contraindications (4), Warnings and Precautions (5.1)and Use in Specific Populations (8.1, 8.3, 8.4)] .

Trial 1 and Trial 2

Trial 1 and Trial 2 were both randomized, placebo-controlled trials evaluating the efficacy and safety of VIVJOA in the reduction of RVVC. Both trials consisted of two phases: an open-label induction phase and an 11-week maintenance phase. Patients received three sequential doses of 150 mg of fluconazole (every 72 hours) on Days, 1, 4 and 7 during the induction phase. Patients returned 14 days after the first dose of fluconazole and if the acute VVC episode was resolved (vulvovaginal signs and symptoms score < 3) they were randomized (2:1) to receive either 150 mg of VIVJOA or placebo for 7 days followed by 11 weekly doses in the maintenance phase.

In Trial 1, a total of 483 patients were enrolled in the induction phase with 326 patients entering the maintenance phase with 217 patients randomized to VIVJOA and 109 patients randomized to placebo. A total of 182 patients (84%) in the VIVJOA group and 91 patients (83%) in the placebo group completed the trial. The mean age of patients was 34 years old (range 17-78 years old) with 85% of patients aged 18-44 years and 15% of patients aged 45 years and older. Patients were 72% White, 13% Black or African American, 14% Asian, and 8% were of Hispanic or Latino ethnicity.

In Trial 2, a total of 425 patients were enrolled into the induction phase with 330 patients entering the maintenance phase with 220 subjects randomized to VIVJOA and 110 patients randomized to placebo. A total of 191 patients (87%) in the VIVJOA group and 91 patients (83%) in the placebo group completed the trial. The mean age of patients was 34 years old (range 18-73 years old) with 85% of patients aged 18-44 years and 15% of patients aged 45 years and older. Patients were 89% White, 10% Black or African American and 15% were of Hispanic or Latino ethnicity.

For both Trial 1 and Trial 2, efficacy was assessed by the proportion of patients with ≥1 culture-verified acute VVC episode (positive fungal culture for Candidaspecies associated with a clinical signs and symptoms score of ≥3) during the Maintenance Phase through Week 48. Evaluation of clinical signs and symptoms included erythema (redness), edema (swelling), excoriation (skin picking), itching, burning and irritation. Since treatment for acute VVC was allowed to be provided to a patient if it was deemed to be clinically needed when the patient had a signs and symptoms score ≥ 3 and a positive KOH test, the proportion of patients with ≥1 culture-verified acute VVC episode or who took medication known to treat VVC during the Maintenance Phase through Week 48 is also presented.

VIVJOA was superior to placebo with reference to the proportion of patients with ≥1 culture-verified acute VVC episode through Week 48 (Table 2) or the proportion of patients with ≥1 culture-verified acute VVC episode or who took medication known to treat VVC during the Maintenance Phase through Week 48. For both Trial 1 and Trial 2, the average percentage of patients was lower in the VIVJOA groups compared with the placebo group (Table 2).

Table 2: Trial 1 and 2 Efficacy Endpoints: ITT Population
 | Trial 1 |  | Trial 2
 | VIVJOA (N=217) | Placebo (N=109) | VIVJOA (N=218) | Placebo (N=108)
Proportion of Patients with ≥1 Culture-verified Acute VVC Episode (Day 1 through Week 48) [Average %. Missing values were imputed with multiple imputation using the following auxiliary information: region, treatment, Baseline body mass index, Baseline age, ethnicity, and visit.] | 6.7% | 42.8% | 3.9% | 39.4%
Treatment Difference p-value [The p-value was obtained using a Chi-square test comparing VIVJOA with placebo.] | <0.001 |  | <0.001
Proportion of Patients with ≥1 Culture-verified Acute VVC Episode or received VVC medication (Day 1 through Week 48) | 27.3% | 50.8% | 21.3% | 49.7%
Treatment Difference p-value | <0.001 |  | <0.001
Abbreviations: ITT=Intent-to-Treat (Population); VVC=vulvovaginal candidiasis.

Trial 3

Trial 3 was a randomized, double-blind trial evaluating the efficacy and safety of VIVJOA versus fluconazole and placebo in adults and post-menarchal pediatric females with RVVC. The trial consisted of two phases: induction and maintenance.

During the induction phase, patients received 1050 mg of VIVJOA over two days (600 mg [4×150mg] on Day 1 and 450 mg [3×150mg] on Day 2) or three sequential doses of 150 mg of fluconazole (every 72 hours) on Days, 1, 4 and 7. Patients returned 14 days after the first dose and moved to the maintenance phase if the acute VVC episode was resolved. During the maintenance phase, patients received 150 mg VIVJOA weekly or placebo weekly for 11 weeks.

A total of 219 patients were randomized (2:1) into the induction phase: 147 to VIVJOA and 72 to fluconazole/placebo. One patient in the VIVJOA group did not receive drug therefore 146 patients received VIVJOA. A total of 112 patients (76%) in the VIVJOA group and 55 patients (76%) in the fluconazole/placebo group completed the trial.

The mean age of patients was 35 years (range 16-78) with 80% of patients aged 18-44 years and 19% of patients aged 45 years and older. Patients were 59% White, 34% Black or African American, 1% Asian and 26% were of Hispanic or Latino ethnicity. The trial was conducted completely in the United States.

Efficacy was assessed by the proportion of patients with ≥1 culture verified acute VVC episode during the maintenance phase (post-randomization through Week 50) or who failed clearing their infection during the induction phase. A recurring acute VVC episode was defined as a positive culture for Candidaspecies and a clinical signs and symptoms score of ≥3. Evaluation of clinical signs and symptoms included erythema(redness), edema (swelling), excoriation (skin picking), itching, burning and irritation. Additionally, the proportion of patients with ≥1 culture verified acute VVC episode or who took medication known to treat VVC during the maintenance phase (post-randomization through Week 50) or who failed clearing their infection during the induction phase is presented.

VIVJOA was superior to fluconazole/placebo in the proportion of patients with ≥1 culture-verified recurring acute VVC episode during the maintenance phase (post randomization through Week 50) or failed clearing their infection during the induction phase and the proportion of patients with ≥1 culture-verified recurring acute VVC episode or took VVC medication known to treat VVC during the maintenance phase (post randomization through Week 50) or who failed clearing their infection during the induction phase. The average percentage of patients was lower in the VIVJOA group compared with the fluconazole/placebo group (Table 3).

Table 3: Trial 3 Efficacy Endpoints ITT population
 | VIVJOA (N=147) | Fluconazole/Placebo (N=72) | Treatment Difference p-value [The p-value was obtained using a Chi-square test comparing VIVJOA with fluconazole/placebo.]
Proportion of Patients with ≥1 Culture-verified Acute VVC Episode through Week 50 or Unresolved VVC Episode During the Induction Phase [Average %, Missing values were imputed with multiple imputation using the following auxiliary information: treatment, baseline body mass index, baseline age, ethnicity, and visit.] | 10.3% | 42.9% | <0.001
Proportion of Patients with ≥1 Culture-verified Acute VVC Episode or took VVC medication through Week 50 or Unresolved VVC Episode During the Induction Phase | 43.5% | 59.0% | 0.039
Abbreviations: ITT=Intent-to-Treat (Population); VVC=vulvovaginal candidiasis

16 HOW SUPPLIED/STORAGE AND HANDLING

16.1 How Supplied

VIVJOA (oteseconazole capsules) are supplied as lavender hard gelatin capsules. Printed black "OTE 150" on the capsule and contain 150 mg oteseconazole. They are available in an 18-count (NDC 74695-823-18) blister package within a child resistant wallet. There will be one blister pack per wallet and one wallet per outer carton.

The fluconazole/VIVJOA dosage regimen is in an 18-count (NDC 74695-945-18) blister package within a child resistant wallet. There is one blister pack of VIVJOA (oteseconazole capsules) per wallet and one wallet per outer carton. The outer carton and wallet contain the following: "fluconazole/VIVJOA dosage regimen" and "fluconazole is prescribed separately".

Fluconazole is not supplied in the carton.

16.2 Storage and Handling

Store at 20°C to 25°C (68°F to 77°F); excursions permitted between 15°C and 30°C (59°F to 86°F) [ See USP Controlled Room Temperature]. Protect from light when removed from the outer carton.

17 PATIENT COUNSELING INFORMATION

Advise the patient to read the FDA-approved patient labeling (Patient Information).

Embryo-Fetal Toxicity

Advise patients that VIVJOA is contraindicated in females of reproductive potential and in pregnant women because it may cause fetal harm [see Contraindications (4), Warnings and Precautions (5.1)and Use in Specific Populations (8.1, 8.3)] .

Lactation

Advise patients that VIVJOA is contraindicated in lactating women because it may cause harm to the breastfed infant [see Contraindications (4), Warnings and Precautions (5.1)and Use in Specific Populations (8.2)].

Important Administration Instructions

Advise patients that VIVJOA must be taken with food, and that capsules must be swallowed whole and not chewed, crushed, dissolved, or opened [see Dosage and Administration (2.1)].

Concomitant Administration with BCRP Transporter Substrates

Advise patients to inform their health care provider if they are taking a BCRP substrate (e.g., rosuvastatin). Concomitant use with VIVJOA may increase the exposure of drugs that are BCRP substrates, which may increase the risk of adverse reactions associated with these drugs [see Drug Interactions (7.1)] .

Manufactured for and distributed by:
Mycovia Pharmaceuticals, Inc.
Durham, NC 27703

Patent numbers: 8,236,962, 8,754,227,10,173,998,10,464,921,10,836,740, 9,840,492,10,414,751

PATIENT INFORMATION
VIVJOA™ [viv joe ah]
(oteseconazole)
capsules, for oral use

What is VIVJOA?

- VIVJOA is a prescription medicine used to reduce the risk of vaginal yeast infections that keep coming back (recurrent vulvovaginal candidiasis, RVVC) in females with a history of RVVC.
- VIVJOA should only be taken by females who are not pregnant and who are not able to become pregnant.

It is not known if VIVJOA is safe and effective in females who have not had their first menstrual period.

Do not take VIVJOA if you:

- Are able to become pregnant.
- Are pregnant or plan to become pregnant. VIVJOA may harm your unborn baby. Tell your doctor if you are pregnant, think you might be pregnant, or plan to become pregnant.
- Are breastfeeding or plan to breastfeed. It is not known if VIVJOA passes into your breastmilk.
- Are allergic to oteseconazole or any of the ingredients in VIVJOA. See the end of this Patient Information leaflet for a complete list of ingredients in VIVJOA.

Before you take VIVJOA, tell your doctor about all of your medical conditions, including if you:

- have kidney problems
- have liver problems

Tell your doctor about all the medicines you take,including prescription and over-the-counter medicines, vitamins, and herbal supplements.

Especially tell your doctor if you take medicines called breast cancer resistance protein (BCRP) transporter substrates, including the cholesterol lowering medicine rosuvastatin. Ask your doctor or pharmacist for a list of these medicines if you are not sure. Taking VIVJOA (a BCRP inhibitor) with BCRP transporter substrates may increase the risk of side effects with these medicines.

Know the medicines you take. Keep a list of them to show your doctor and pharmacist when you get a new medicine.

How should I take VIVJOA?

- Your doctor has prescribed VIVJOA:
  - Take VIVJOA exactly as your doctor tells you to take it. Talk to your doctor if you have any questions.
  - On Day 1:Take VIVJOA 600 mg(four capsules as a single dose), by mouth then,
  - On Day 2:Take VIVJOA 450 mg(three capsules as a single dose), by mouth then,
  - On Day 14: Take VIVJOA 150 mg(one capsule) one time a week(every 7 days) by mouth for 11 weeks.
- Take VIVJOA capsules by mouth with food.
- Swallow VIVJOA capsules whole. Do not chew, crush, dissolve, or open the capsules.

What are the possible side effects of VIVJOA?

- See " Do not take VIVJOA if you:" Females who are pregnant, are able to become pregnant, and females who are breastfeeding should not take VIVJOA.

The most common side effects of VIVJOA areheadache and nausea.

These are not all the possible side effects of VIVJOA. For more information, ask your doctor or pharmacist.

Call your doctor for medical advice about side effects. You may report side effects to FDA at 1-800-FDA-1088.

How should I store VIVJOA?

- Store VIVJOA at room temperature between 68°F to 77°F (20°C to 25°C).
- Protect from light when removed from the outer carton.

Keep VIVJOA and all medicines out of the reach of children.

General information about the safe and effective use of VIVJOA.

Medicines are sometimes prescribed for purposes other than those listed in a Patient Information leaflet. Do not use VIVJOA for a condition for which it has not been prescribed. Do not give VIVJOA to other people, even if they have the same symptoms that you have. It may harm them.

You can ask your doctor or pharmacist for information about VIVJOA that is written for health professionals.

What are the ingredients in VIVJOA?

Active Ingredient:oteseconazole

Inactive Ingredients:croscarmellose sodium, hydroxypropyl cellulose, lactose, magnesium stearate, silicified microcrystalline cellulose, and sodium lauryl sulfate. Capsule shell and print constituents: FD&C Blue #1, FD&C Red #3, gelatin, Opacode SW-9008/SW-9009 and titanium dioxide.

VIVJOA does not contain gluten (wheat, barley, or rye).

Manufactured for and Distributed by:
Mycovia Pharmaceuticals, Inc.
Durham, NC 27703
© 2021 Mycovia Pharmaceuticals, Inc. All rights reserved.
For more information, go to www.mycovia.comor call 1-855-299-0637.

This Patient Information has been approved by the U.S. Food and Drug Administration.

Approved: X/2022

PRINCIPAL DISPLAY PANEL - 150 mg Capsule Blister Pack Label

Dosing directions for VIVJOA™ (oteseconazole capsules), 150 mg per capsule, for oral use

▼ START HERE

DAY
1
DAY
1
DAY
1
DAY
1

DAY 1: Take ALL FOUR capsules together.

DAY
2
DAY
2
DAY
2

DAY 2: Take ALL THREE capsules together.

WEEK
2
WEEK
3
WEEK
4

Beginning on DAY 14, take ONE capsule weekly.

WEEK
5
WEEK
6
WEEK
7

To remove capsule, press from the reverse side.

WEEK
8
WEEK
9
WEEK
10

Manufactured for Mycovia Pharmaceuticals, Inc. by Patheon.

WEEK
11
WEEK
12

Distributed by Mycovia Pharmaceuticals, Inc.

Rx ONLY

LOT XXXXX0000
EXP MMM YYYY

PRINCIPAL DISPLAY PANEL - 150 mg Capsule Blister Pack Container

NDC 74695-823-18
Rx only

18 CAPSULES

Press and
hold button.

vivjoa™
(oteseconazole capsules)
150 mg per capsule, for oral use

See package insert for full Prescribing Information.

STEP 1 Press and hold button.

STEP 2 Pull out medication card.

Pull out here.
▼

PRINCIPAL DISPLAY PANEL - 150 mg Capsule Blister Pack Container Carton

NDC 74695-823-18
Rx only

See package insert for full Prescribing Information.

vivjoa™
(oteseconazole capsules)

150 mg per capsule, for oral use

18 CAPSULES